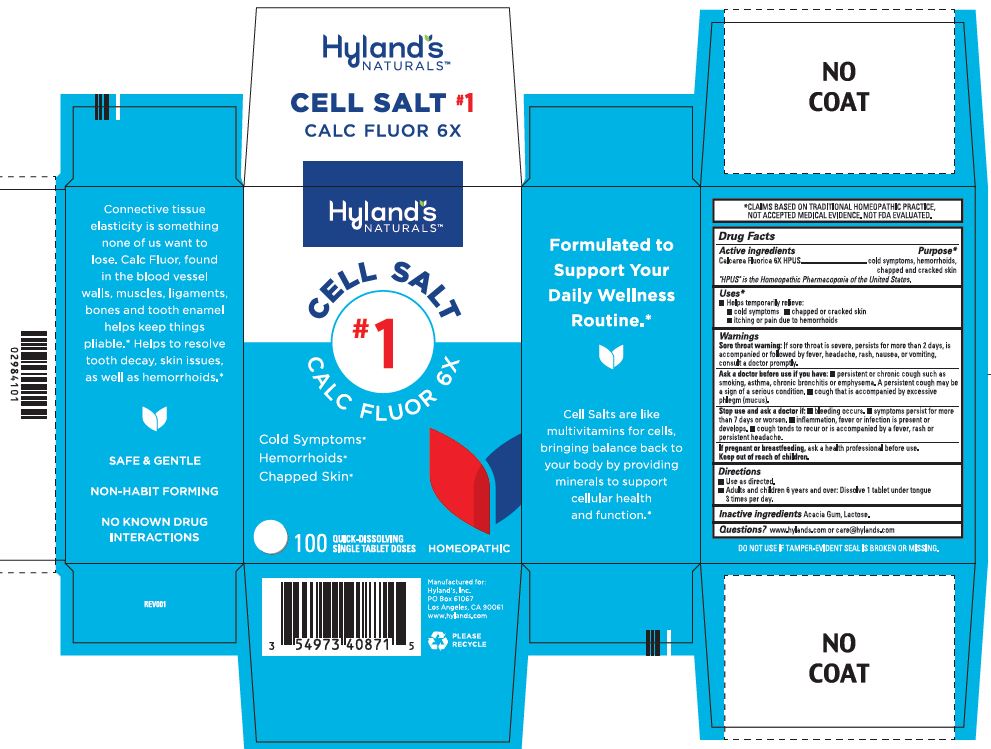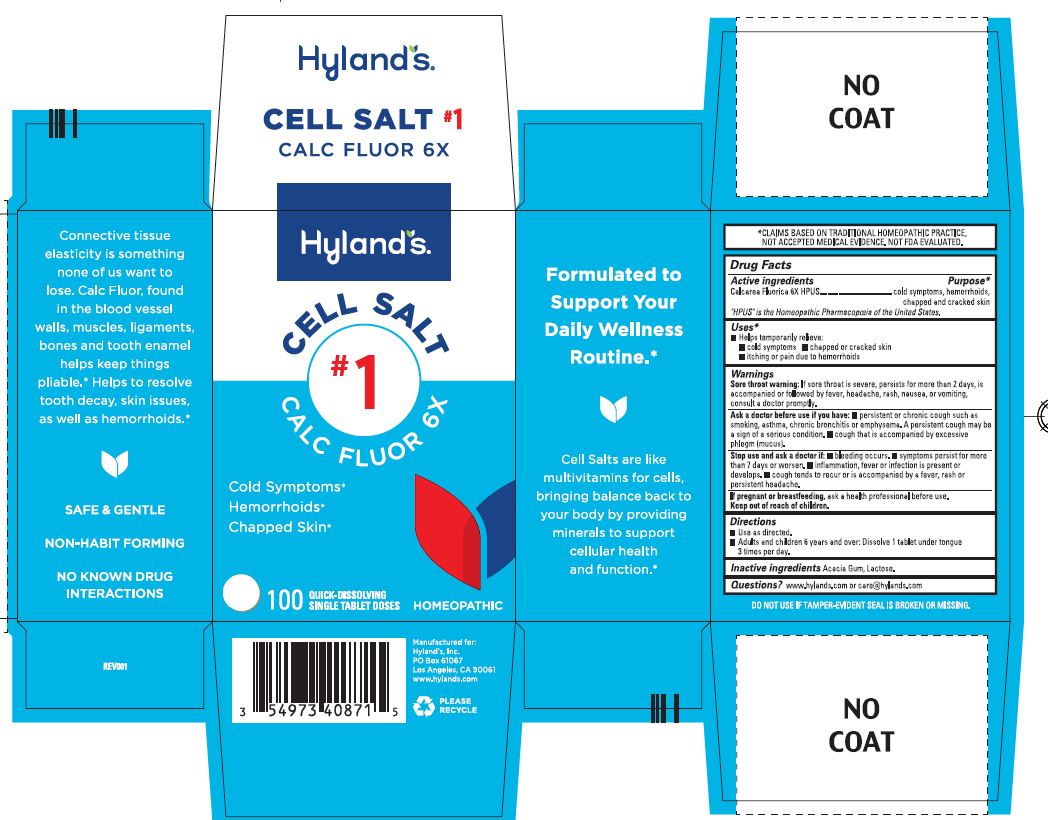 DRUG LABEL: CALC FLUOR 6X
NDC: 54973-4087 | Form: TABLET, SOLUBLE
Manufacturer: Hyland's Inc.
Category: homeopathic | Type: HUMAN OTC DRUG LABEL
Date: 20250410

ACTIVE INGREDIENTS: CALCIUM FLUORIDE 6 [hp_X]/1 1
INACTIVE INGREDIENTS: ACACIA; LACTOSE MONOHYDRATE

Cell Salt #1 Calc Fluor 6X

PURPOSE

Cold Symptoms

Hemorrhoid

Chapped Skin

Drug Facts

Active ingredients | Purpose
Calcarea Fluorica 6X HPUS | cold symptoms, hemorrhoids, chapped and cracked skin

"HPUS" is the Homeopathic Pharmacopoeia of the United States.

Uses

■Temporarily relieves:
■ cold symptoms ■ chapped or cracked skin
■ itching or pain due to hemorrhoids

Warnings

Sore throat warning

If sore throat is severe, persists for more than 2 days, is accompanied or followed by fever, headache, rash, nausea, or vomiting,
consult a doctor promptly.

Ask a doctor before use if you have

■ persistent or chronic cough such as smoking, asthma, chronic bronchitis or emphysema. A persistent cough may be a sign of a serious condition. ■ cough that is accompanied by excessive phlegm (mucus).

Stop use and ask a doctor if

■ bleeding occurs. ■ symptoms persist for more than 7 days or worsen. ■ inflammation, fever or infection is present or develops.

■ cough tends to recur or is accompanied by a fever, rash or persistent headache.

If pregnant or breastfeeding

Ask a health professional before use.

Directions

■ Use as directed.
■ Adults and children 6 years and over: Dissolve 1 tablet under tongue 3 times per day.

Inactive ingredients

Acacia Gum, Lactose.

Questions?

www.hylands.com or care@hylands.com

PACKAGE LABEL - 100 TABLETS BOTTLE CARTON

Hyland's

NATURALS™

CELL SALT

#1

CALC FLOUR 6X

Cold Symptoms*

Hemorrhoids*

Chapped Skin*

100

QUICK - DISSOLVING

SINGLE TABLET DOSES

HOMEOPATHIC